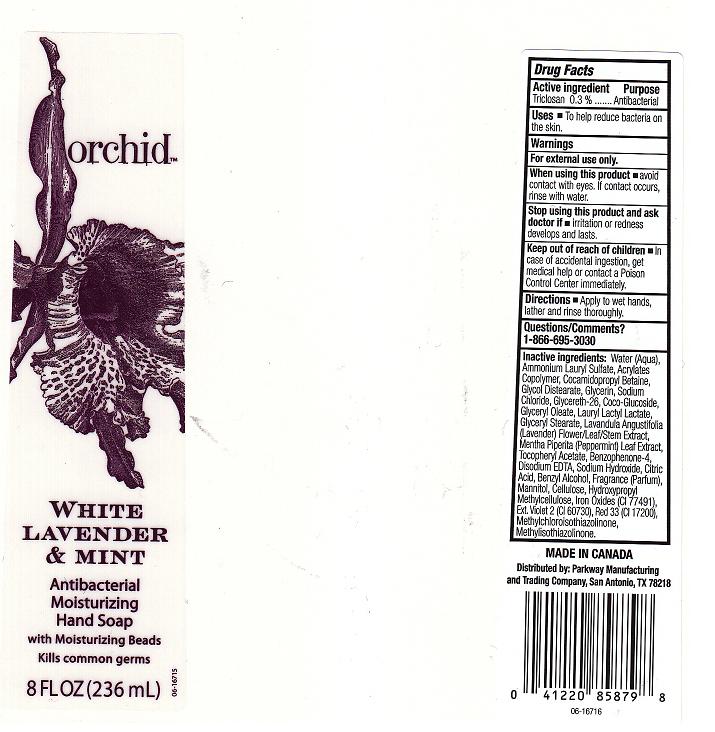 DRUG LABEL: WHITE LAVENDER AND MINT ANTIBACTERIAL MOISTURIZING HAND SP
NDC: 37808-292 | Form: LIQUID
Manufacturer: H E B
Category: otc | Type: HUMAN OTC DRUG LABEL
Date: 20110104

ACTIVE INGREDIENTS: TRICLOSAN 0.3 mL/100 mL
INACTIVE INGREDIENTS: WATER; AMMONIUM LAURYL SULFATE; CARBOMER COPOLYMER TYPE A; COCAMIDOPROPYL BETAINE; GLYCOL DISTEARATE; GLYCERIN; SODIUM CHLORIDE; GLYCERETH-26; COCO GLUCOSIDE; GLYCERYL MONOOLEATE; LAURYL LACTATE; GLYCERYL MONOSTEARATE; LAVANDULA ANGUSTIFOLIA FLOWERING TOP; MENTHA PIPERITA LEAF; .ALPHA.-TOCOPHEROL ACETATE, D-; SULISOBENZONE; EDETATE DISODIUM; SODIUM HYDROXIDE; ANHYDROUS CITRIC ACID; BENZYL ALCOHOL; MANNITOL; POWDERED CELLULOSE; HYPROMELLOSES; FERRIC OXIDE RED; EXT. D&C VIOLET NO. 2; D&C RED NO. 33; METHYLCHLOROISOTHIAZOLINONE; METHYLISOTHIAZOLINONE

DRUG FACTS

ACTIVE INGREDIENT

TRICLOSAN 0.3 PERCENT

PURPOSE

ANTIBACTERIAL

USES

TO HELP REDUCE BACTERIA ON THE SKIN.

WARNINGS

FOR EXTERNAL USE ONLY.

WHEN USING THIS PRODUCT

AVOID CONTACT WITH EYES. IF CONTACT OCCURS, RINSE WITH WATER.

STOP USING THIS PRODUCT AND ASK DOCTOR IF

IRRITATION OR REDNESS DEVELOPS AND LASTS.

KEEP OUT OF REACH OF CHILDREN

IN CASE OF ACCIDENTAL INGESTION, GET MEDICAL HELP OR CONTACT A POISON CONTROL CENTER IMMEDIATELY.

DIRECTIONS

APPLY TO WET HANDS, LATHER AND RINSE THOROUGHLY.

QUESTIONS OR COMMENTS

1-866-695-3030

INACTIVE INGREDIENTS

WATER, AMMONIUM LAURYL SULFATE, ACRYLATES COPOLYMER, COCAMIDOPROPYL BETAINE, GLYCOL DISTEARATE, GLYCERIN, SODIUM CHLORIDE, GLYCERETH-26, COCO-GLUCOSIDE, GLYCERYL OLEATE, LAURYL LACTYL LACTATE, GLYCERYL STEARATE, LAVENDULA ANGUSTIFOLIA (LAVENDER) FLOWER/LEAF/STEM EXTRACT, MENTHA PIPERITA (PEPPERMINT) LEAF EXTRACT, TOCOPHERYL ACETATE, BENZOPHENONE-4, DISODIUM EDTA, SODIUM HYDROXIDE, CITRIC ACID, BENZYL ALCOHOL, FRAGRANCE, MANNITOL, CELLULOSE, HYDROXYPROPYL METHYLCELLULOSE, IRON OXIDES (CI 77491), EXT. VIOLET 2 (CI 60730), RED 33 (CI 17200), METHYLCHLOROISOTHIAZOLINONE, METHYLISOTHIAZOLINONE.